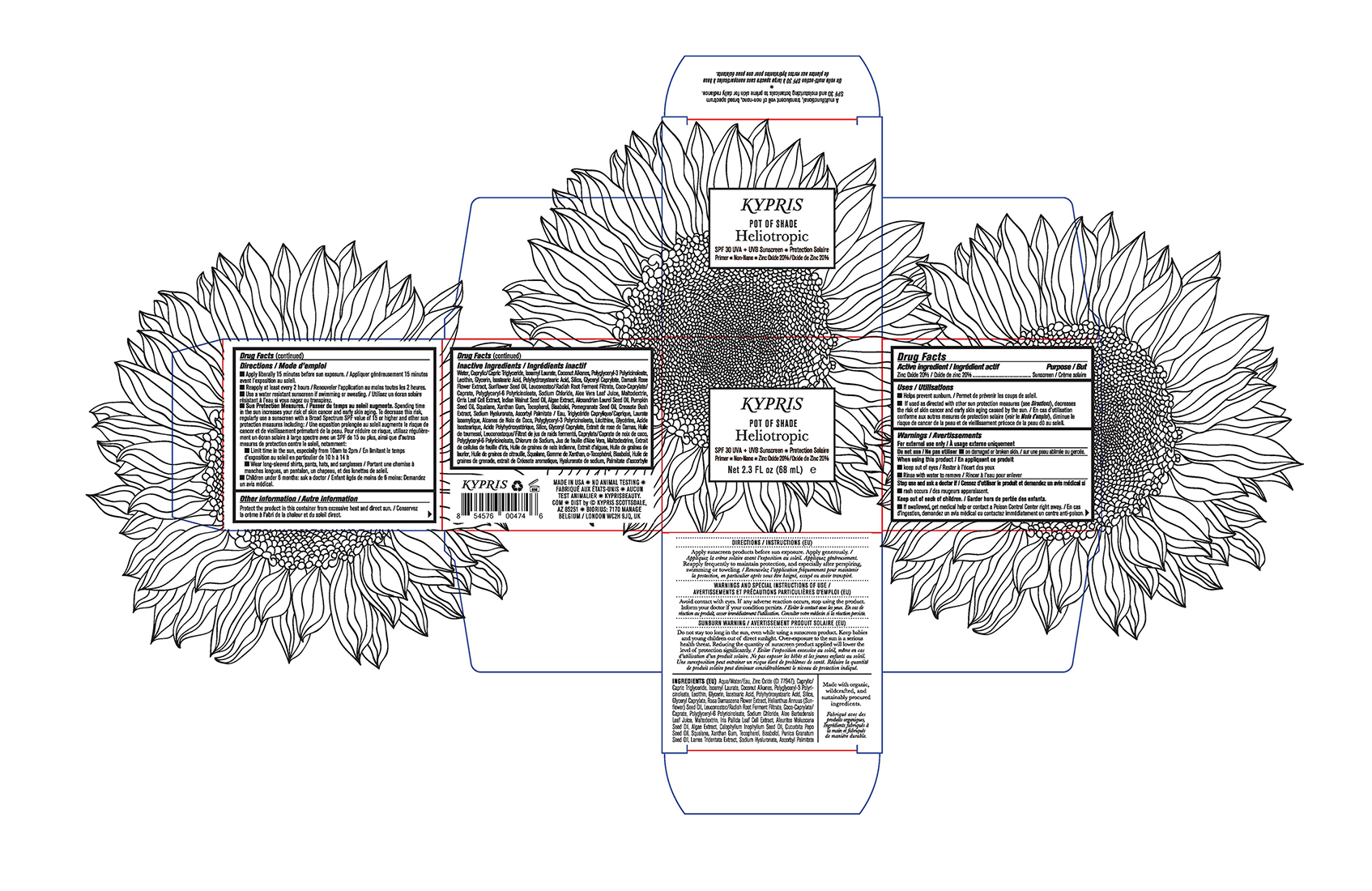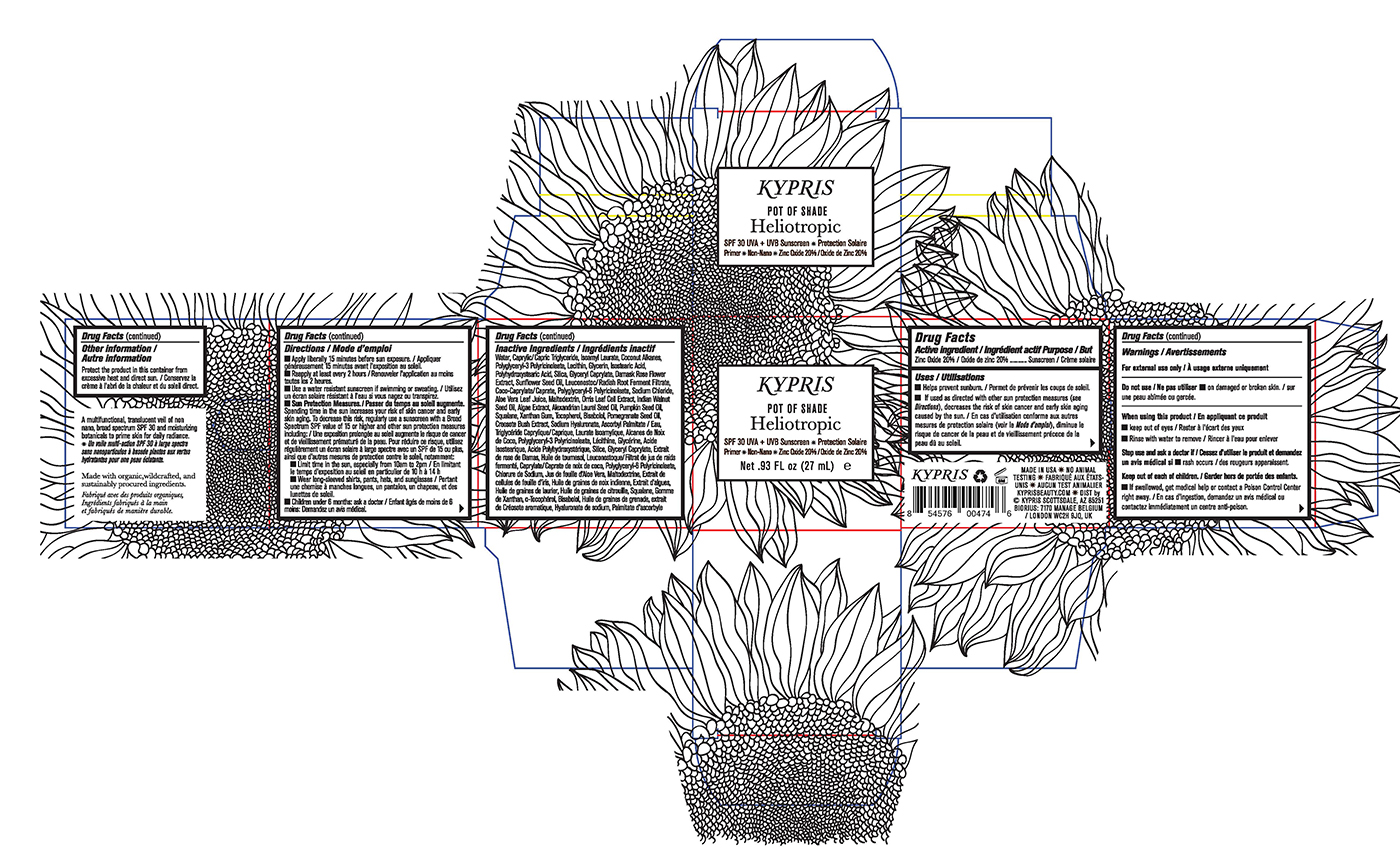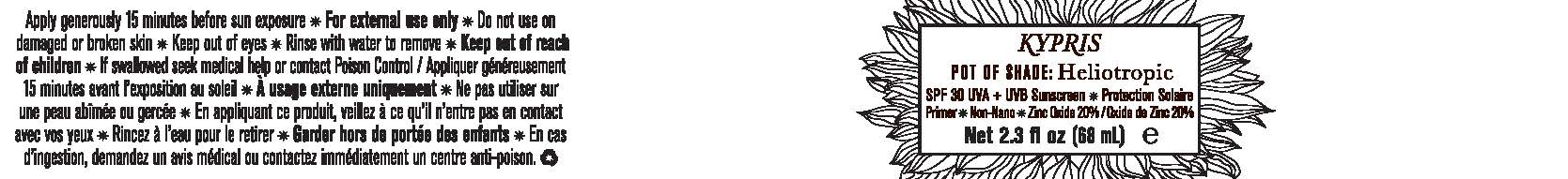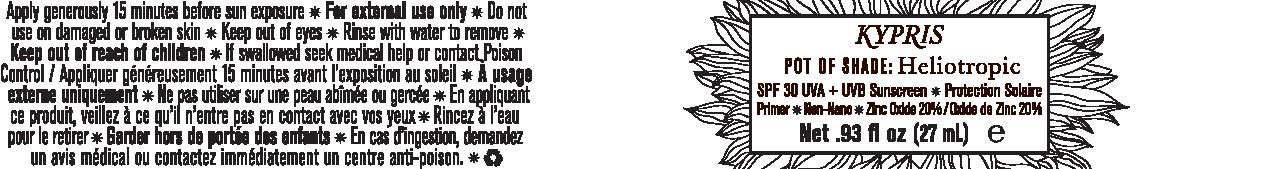 DRUG LABEL: Cream
NDC: 61354-030 | Form: CREAM
Manufacturer: Oxygen Development LLC
Category: otc | Type: HUMAN OTC DRUG LABEL
Date: 20230210

ACTIVE INGREDIENTS: ZINC OXIDE 19.72 mg/100 mg
INACTIVE INGREDIENTS: POLYGLYCERYL-3 PENTARICINOLEATE; WATER; LECITHIN, SOYBEAN; COCONUT ALKANES; GLYCERIN; MEDIUM-CHAIN TRIGLYCERIDES; SODIUM CHLORIDE; SUNFLOWER OIL; GLYCERYL CAPRATE; SILICON DIOXIDE; POLYGLYCERYL-6 POLYRICINOLEATE; ISOAMYL LAURATE; ROSA DAMASCENA FLOWER; ISOSTEARIC ACID; POLYHYDROXYSTEARIC ACID (2300 MW)

KYPRIS POT OF SHADE HELIOTROPIC SPF 30 UVA+UVB SUNSCREEN PROTECTION SOLAIRE PRIMER

Active Ingredient

Zinc Oxide 20%

Purpose

Sunscreen

Uses

Helps prevent sunburn
If uses as directed with other sun protection measures (see Directions), decreases the risk of skin cancer and early skin aging caused by the sun.

Warnings

For external use only.

Do not use

on damaged or broken skin.

When using this product

keep out of eyes
Rinse with water to remove

Stop use and ask a doctor if

rash occurs

Keep out of reach of children

If swallowed, get medical help or contact a Poison Control Center right away.

Directions

Apply liberally 15 minutes before sun exposure.
Reapply at least every 2 hours
Use a water resistant sunscreen if swimming or sweating.
Sun Protection Measures. Spending time in the sun increases your risk of skin cancer and early skin aging. To decrease this risk, regularly use a sunscreen with a Broad Spectrum SPF value of 15 or higher and other sun protection measures including:
Limit time in the sun, especially from 10am to 2 pm
Wear long-sleeved shirts, pants, hats, and sunglasses
Children under 6 months: ask a doctor

Other information

Protect the product in this container from excessive heat and direct sun.

Inactive Ingredients

Water, Caprylic/Capric Triglyceride, Isoamyl Laurate, Coconut Alkanes, Polyglyceryl-3 Polyricinoleate, Lecithin, Glycerin, Isostearic Acid, Polyhydroxystearic Acid, Silica, Glyceryl Caprylate, Damask Rose Flower Extract, Sunflower Seed Oil, Leuconostoc/Radish Root Ferment Filtrate, Coco-Caprylate/Caprate, Polyglyceryl-6 Polyricinoleate, Sodium Chloride, Aloe Vera Leaf Juice, Maltodextrin, Orris Leaf Cell Extract, Indian Walnut Seed Oil, Algae Extract, Alexandrian Laurel Seed Oil, Pumpkin Seed Oil, Squalane, Xanthan Gum, Tocopherol, Bisabolol, Pomegranate Seed Oil, Creosote Bush Extract, Sodium Hyaluronate, Ascorbyl Palmitate.